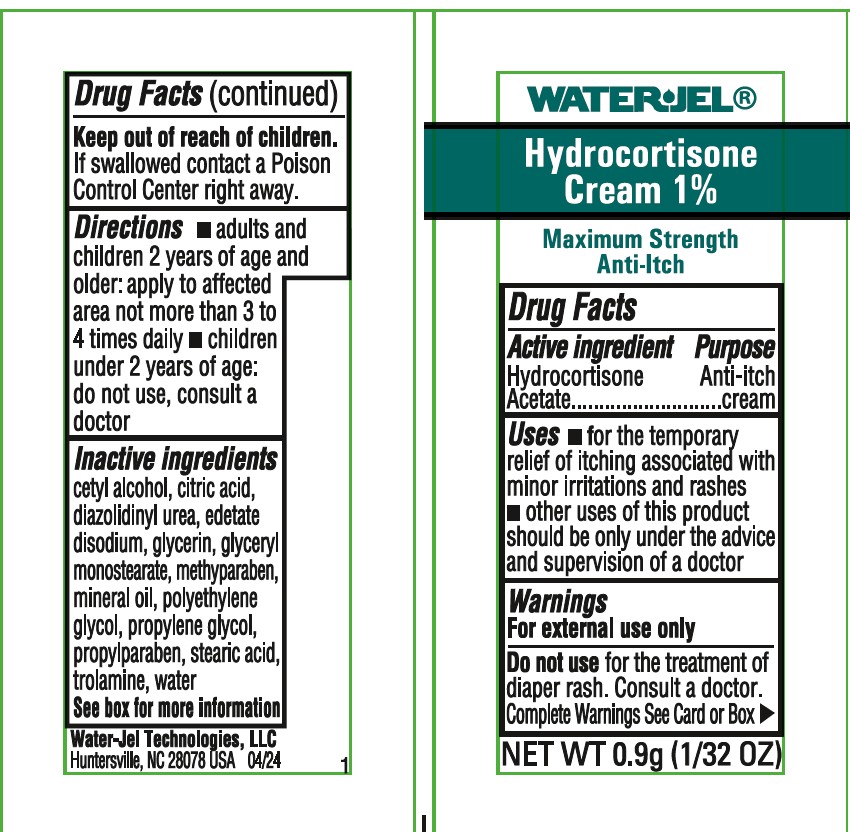 DRUG LABEL: HYDROCORTISONE
NDC: 59898-800 | Form: OINTMENT
Manufacturer: Water-Jel Technologies
Category: otc | Type: HUMAN OTC DRUG LABEL
Date: 20251231

ACTIVE INGREDIENTS: HYDROCORTISONE ACETATE 1 g/100 g
INACTIVE INGREDIENTS: EDETATE DISODIUM; LIGHT MINERAL OIL; STEARIC ACID; GLYCERYL MONOSTEARATE; POLYETHYLENE GLYCOL, UNSPECIFIED; CETYL ALCOHOL; TROLAMINE; METHYLPARABEN; PROPYLENE  GLYCOL; DIAZOLIDINYL UREA; PROPYLPARABEN; GLYCERIN; WATER

1% Hydrocortisone Cream

Active ingredient

Hydrocortisone acetate (equivalent to Hydrocortisone 1%)

Purpose

Anti-itch cream

Uses

- for the temporary relief of itching associated with minor skin irritations and rashes
- other uses of this product should be only under the advice and supervision of a doctor

Warnings

For external use only

Do not use

for the treatment of diaper rash. Consult a doctor

When using this product

- avoid contact with eyes
- do not begin use of any other hydrocortisone product unless you've consulted a doctor

Stop use and ask a doctor if

- condition worsens
- symptoms persist more than 7 days
- condition clears up and occurs again within a few days

Keep out of the reach of children

If swallowed, get medical help or contact a Poison Control Center right away.

Directions

- adults and children 2 years of age and older: apply to affected area not more than 3 to 4 times daily
- children under 2 years; do not use, consult a doctor

Other information

- clean the affected area
- store at room temperature
- do not use any opened or torn packets
- you may report a serious adverse reaction to this product to 855-428-6074

Inactive ingredients

cetyl alcohol, citric acid, diazolidinyl urea, edetate disodium, glycerin, glyceryl monostearate, methylparaben, mineral oil, polyethylene glycol, propylene glycol, propylparaben, stearic acid, trolamine, water

Questions ?

855-428-6074

www.safeguardmedical.com